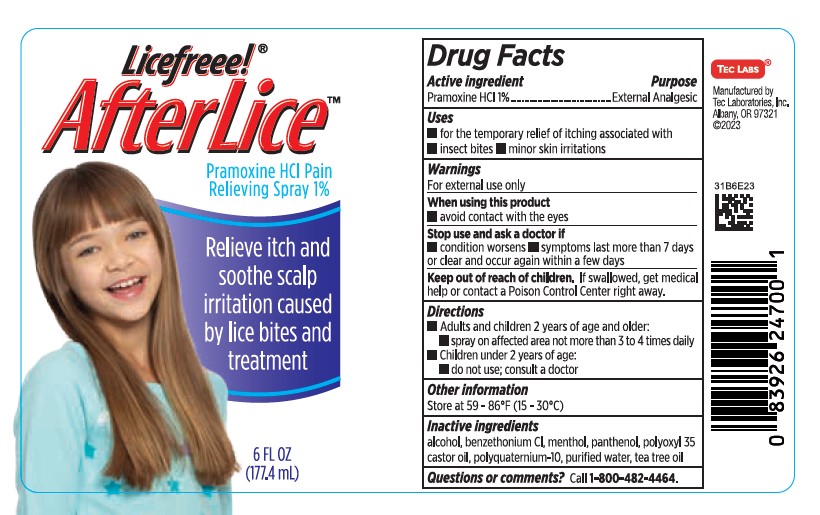 DRUG LABEL: Licefreee AfterLice
NDC: 51879-260 | Form: SPRAY
Manufacturer: Tec Laboratories Inc.
Category: otc | Type: HUMAN OTC DRUG LABEL
Date: 20241105

ACTIVE INGREDIENTS: PRAMOXINE HYDROCHLORIDE 10 mg/1 g
INACTIVE INGREDIENTS: TEA TREE OIL; BENZETHONIUM CHLORIDE; MENTHOL; POLYOXYL 35 CASTOR OIL; ALCOHOL; WATER; PANTHENOL; POLYQUATERNIUM-10 (400 CPS AT 2%)

LiceFreee AfterLice Spray

Active ingredient

Pramoxine HCI 1%

WARNINGS

For external use only

When using this product

- avoid contact with eyes

Stop use and ask a doctor if

- condition worstens
- symptoms last more than 7 days or clear up and occur again within a few days

Keep out of reach of children

- If swallowed, get medical help or contact a Poison Control Center right away.

Other Information

Store at 59-86ºF (15-30ºC)

Inactive ingredients

alcohol, benzethonium CI, menthol, panthenol, polyoxyl 35 castor oil, polyquaternium-10, purified water, tea tree oil

Questions or comments?

Call 1-800-482-4464.

Uses

for the temporary relief of itching associated with

- insect bites
- minor skin irritations

Directions

- Adults and children 2 years of age and older: spray on affected area not more than 3-4 times daily
- Children under 2 years; do not use; consult a doctor

PURPOSE

Pain and itch relief spray for scalp irritation caused by lice bites and lice treatments.